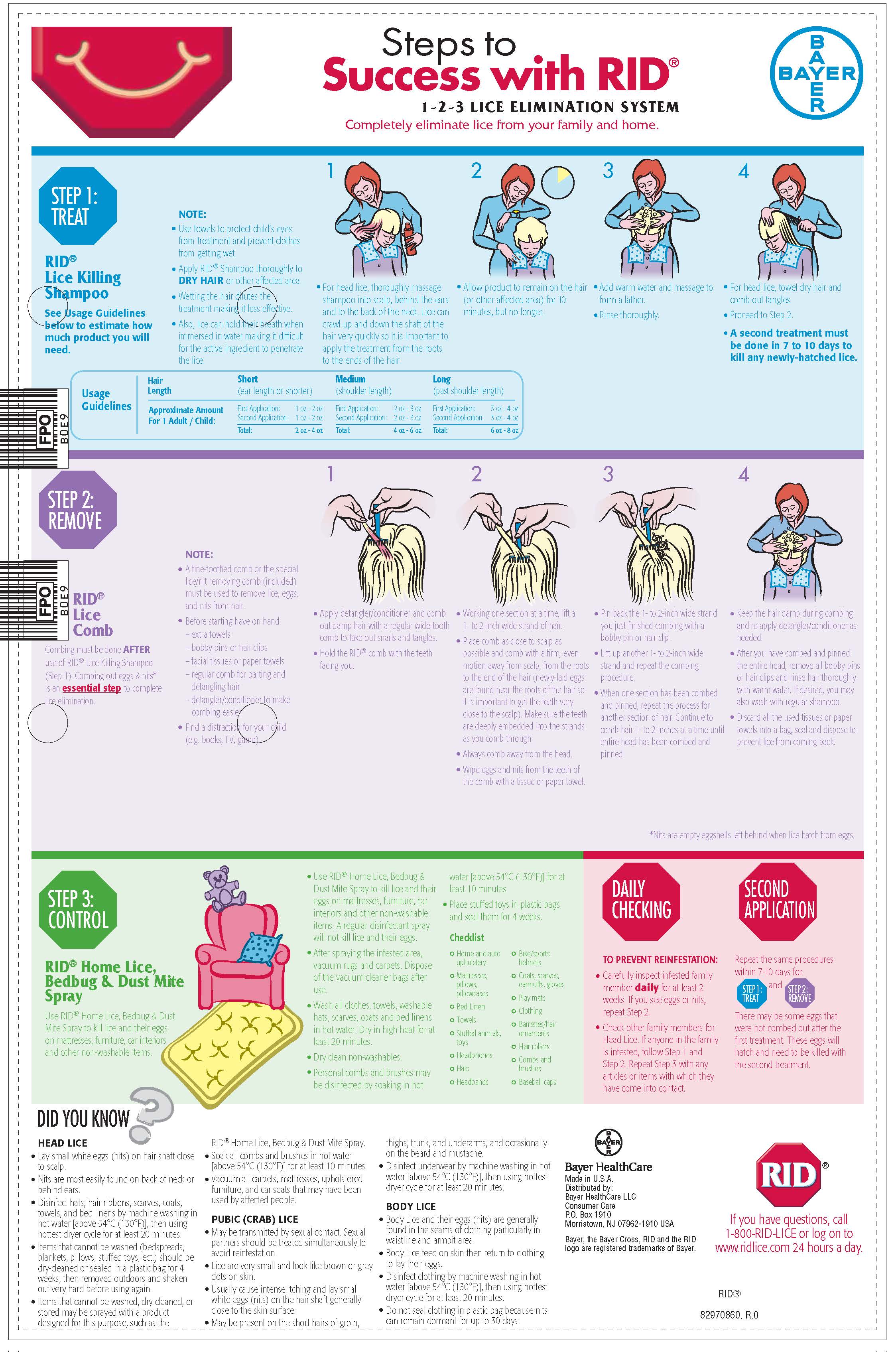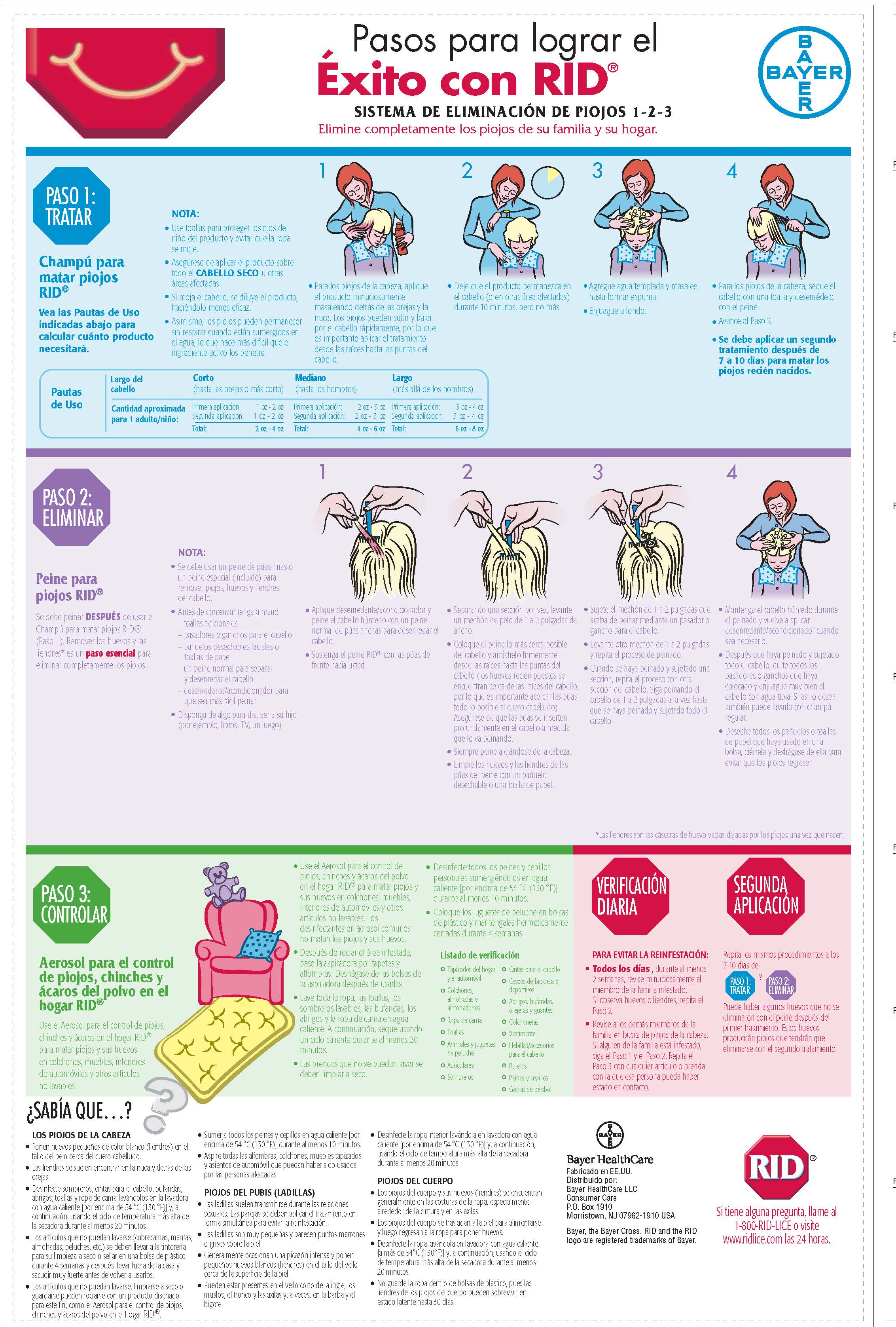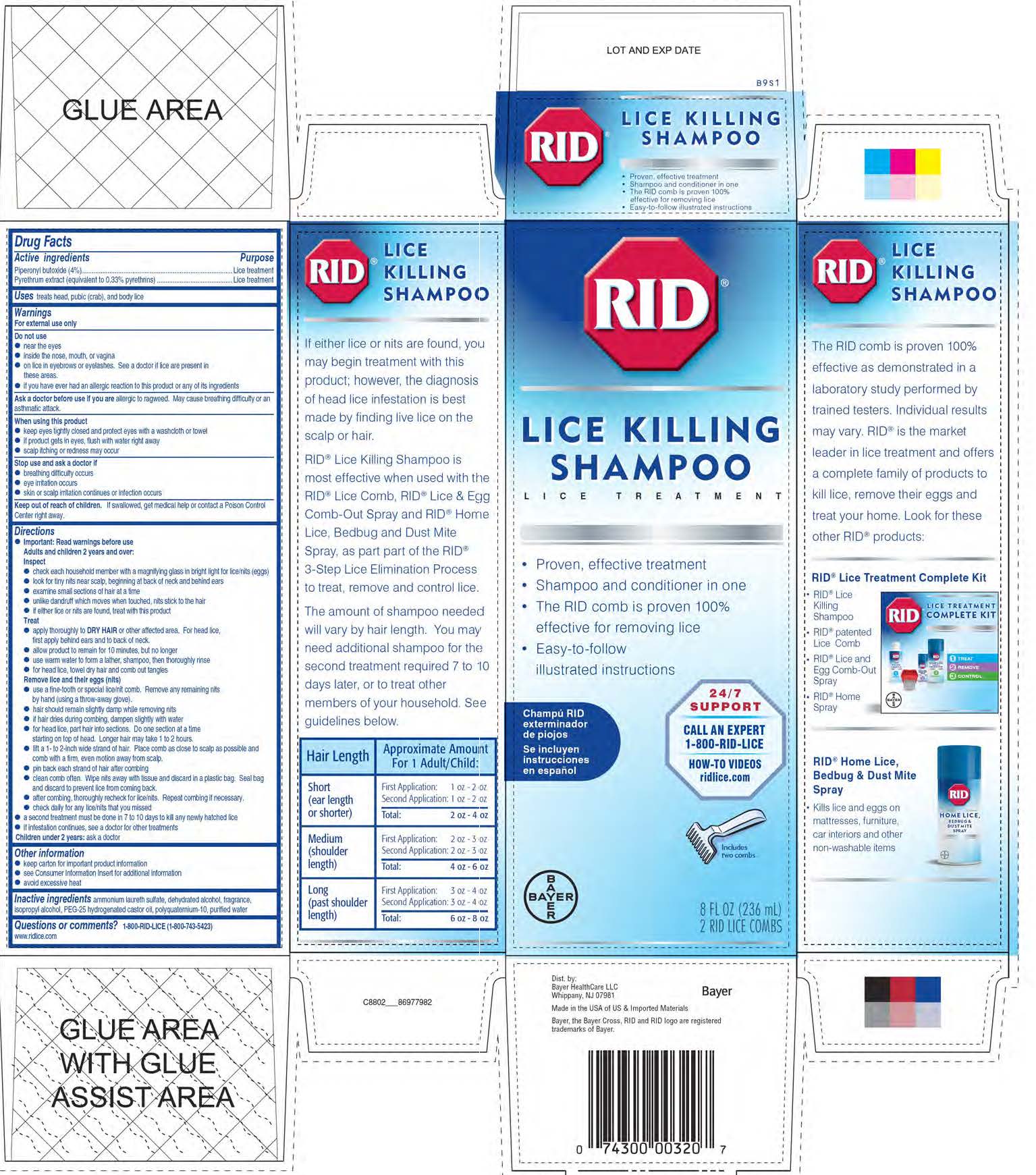 DRUG LABEL: RID Lice Killing
NDC: 0280-9000 | Form: SHAMPOO
Manufacturer: Bayer HealthCare LLC.
Category: otc | Type: HUMAN OTC DRUG LABEL
Date: 20190808

ACTIVE INGREDIENTS: PIPERONYL BUTOXIDE 40 mg/1 mL; PYRETHRUM EXTRACT 3.3 mg/1 mL
INACTIVE INGREDIENTS: PEG-25 HYDROGENATED CASTOR OIL; POLYQUATERNIUM-10 (125 MPA.S AT 2%); AMMONIUM LAURETH-2 SULFATE; WATER; ISOPROPYL ALCOHOL

RID Lice Killing Shampoo

Drug Facts

Active ingredients

Piperonyl butoxide (4%)

Pyrethrum extract (equivalent to 0.33% pyrethrins)

Purpose

Lice treatment

Uses

Uses treats head, pubic (crab), and body lice

Warnings

For external use only

Do not use

· near the eyes

· inside the nose, mouth, or vagina

· on lice in eyebrows or eyelashes. See a doctor if lice are present in these areas.

· if you have ever had an allergic reaction to this product or any of its ingredients

Ask a doctor before use if you are allergic to ragweed. May cause breathing difficulty or an asthmatic attack.

When using this product

● keep eyes tightly closed and protect eyes with a washcloth or towel

● if product gets in eyes, flush with water right away

● scalp itching or redness may occur

Stop use and ask a doctor if

● breathing difficulty occurs

● eye irritation occurs

● skin or scalp irritation continues or infection occurs

Keep out of reach of children. If swallowed, get medical help or contact a Poison Control Center right away.

Directions

● Important: Read warnings before use

Adults and children 2 years and over:

Inspect

● check each household member with a magnifying glass in bright light for lice/nits (eggs)

● look for tiny nits near scalp, beginning at back of neck and behind ears

● examine small sections of hair at a time

● unlike dandruff which moves when touched, nits stick to the hair

● if either lice or nits are found, treat with this product

Treat

● apply thoroughly to DRY HAIR or other affected area. For head lice, first apply behind ears and to back of neck.

● allow product to remain for 10 minutes, but no longer

● use warm water to form a lather, shampoo, then thoroughly

rinse

● for head lice, towel dry hair and comb out tangles

Remove lice and their eggs (nits)

● use a fine-tooth or special lice/nit comb. Remove any remaining nits by hand (using a throw-away glove).

● hair should remain slightly damp while removing nits

● if hair dries during combing, dampen slightly with water

● for head lice, part hair into sections. Do one section at a time starting on top of head. Longer hair may take 1 to 2 hours.

● lift a 1- to 2-inch wide strand of hair. Place comb as close to scalp as possible and comb with a firm, even motion away from scalp.

Other information

● keep carton for important product information

● see Consumer Information Insert for additional information

● avoid excessive heat

INACTIVE INGREDIENT

Inactive ingredients ammonium laureth sulfate, dehydrated alcohol, fragrance, isopropyl alcohol, PEG-25 hydrogenated castor oil, polyquaternium-10, purified water

Questions or comments? 1-800-RID-LICE (1-800-743-5423) www.ridlice.com

PACKAGE LABEL

RID

LICE KILLING

SHAMPOO

LICE TREATMENT

- Proven, effective treatment
- Shampoo and conditioner in one
- The RID comb is proven 100% effective for removing lice
- East-to-follow illustrated instructions

Champu' RID

exterminador

de piojos

Se incluyen

instructiones en espanol

24/7

SUPPORT

CALL AN EXPERT

1-800-RID-LICE

HOW-TO VIDEOS

ridlice.com

Includes

two combs

8 FL OZ (236 mL)

2 RID LICE COMBS